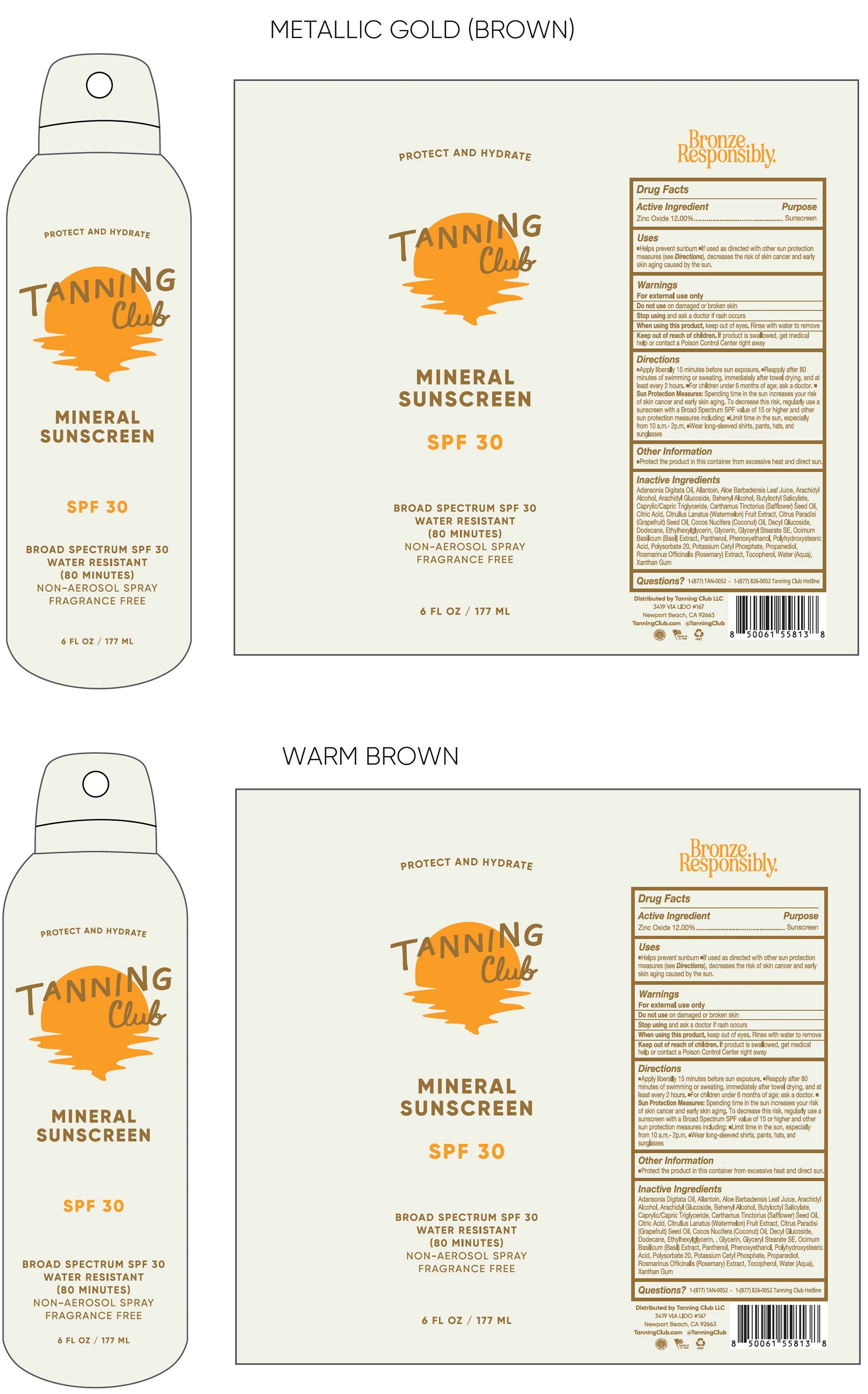 DRUG LABEL: Tanning Club Mineral Sunscreen SPF 30
NDC: 84562-979 | Form: LIQUID
Manufacturer: Tanning Club LLC
Category: otc | Type: HUMAN OTC DRUG LABEL
Date: 20260204

ACTIVE INGREDIENTS: ZINC OXIDE 120 mg/1 mL
INACTIVE INGREDIENTS: ADANSONIA DIGITATA SEED OIL; ALLANTOIN; ALOE VERA LEAF JUICE; ARACHIDYL ALCOHOL; ARACHIDYL GLUCOSIDE; BEHENYL ALCOHOL; BUTYLOCTYL SALICYLATE; MEDIUM-CHAIN TRIGLYCERIDES; SAFFLOWER OIL; CITRIC ACID MONOHYDRATE; WATERMELON; GRAPEFRUIT SEED OIL; COCONUT OIL; DECYL GLUCOSIDE; DODECANE; ETHYLHEXYLGLYCERIN; GLYCERIN; GLYCERYL STEARATE SE; PANTHENOL; PHENOXYETHANOL; POLYSORBATE 20; POTASSIUM CETYL PHOSPHATE; PROPANEDIOL; ROSEMARY; TOCOPHEROL; WATER; XANTHAN GUM

Tanning Club Mineral Sunscreen SPF 30

Active Ingredient

Zinc Oxide 12.00%

Purpose

Sunscreen

Uses

- Helps prevent sunburn.
- If used as directed with other sun protection measures (see Directions), decreases the risk of skin cancer and early skin aging caused by the sun.

Warnings

For external use only

Do not use

on damaged or broken skin

Stop using and ask a doctor if

rash occurs

When using this product,

keep out of eyes. Rinse with water to remove

Keep out of reach of children.

If product is swallowed, get medical help or contact a Poison Control Center right away

Directions

- Apply liberally 15 minutes before sun exposure.
- Reapply after 80 minutes of swimming or sweating, immediately after towel drying, and at least every 2 hours.
- For children under 6 months of age: ask a doctor.
- Sun Protection Measures.Spending time in the sun increases your risk of skin cancer and early skin aging. To decrease the risk, regularly use a sunscreen with a Broad Spectrum SPF value of 15 or higher and other sun protection measures including:
- Limit time in the sun, especially from 10 a.m. - 2p.m.
- Wear long-sleeved shirts, pants, hats, and sunglasses

Other Information

- Protect the product in this container from excessive heat and direct sun.

Inactive Ingredients

Adansonia Digitata Oil, Allantoin, Aloe Barbadensis Leaf Juice, Arachidyl Alcohol, Arachidyl Glucoside, Behenyl Alcohol, Butyloctyl Salicylate, Caprylic/Capric Triglyceride, Carthamus Tinctorius (Safflower) Seed Oil, Citric Acid, Citrullus Lanatus (Watermelon) Fruit Extract, Citrus Paradisi (Grapefruit) Seed Oil, Cocos Nucifera (Coconut) Oil, Decyl Glucoside, Dodecane, Ethylhexylglycerin, Glycerin, Glyceryl Stearate SE, Ocimum Basilicum (Basil) Extract, Panthenol, Phenoxyethanol, Polyhydroxystearic Acid, Polysorbate 20, Potassium Cetyl Phosphate, Propanediol, Rosmarinus Officinalis (Rosemary) Extract, Tocopherol, Water(Aqua), Xanthan Gum

Questions?

1-(877) TAN-0052- 1-(877) 826-0052 Tanning Club Hotline